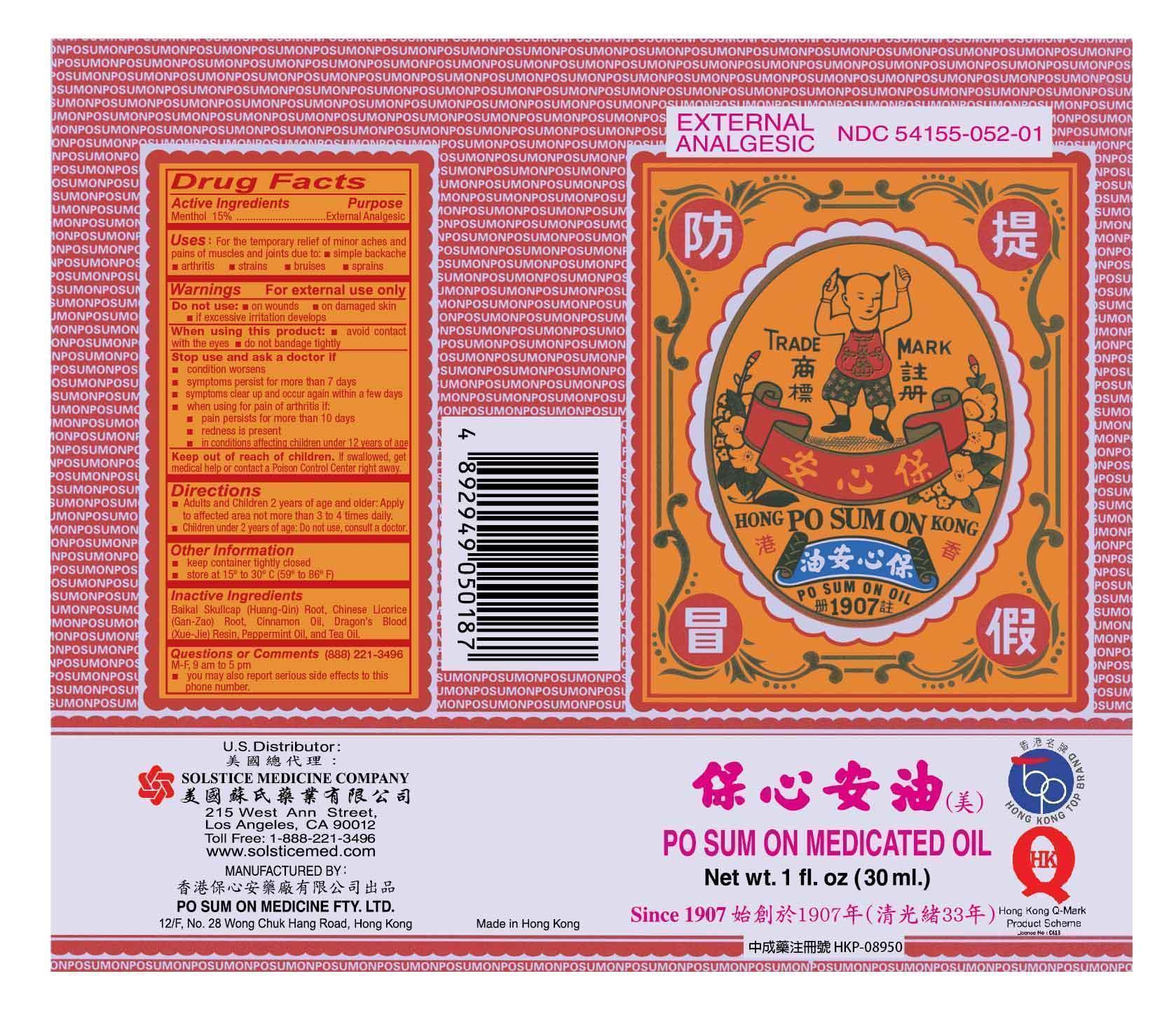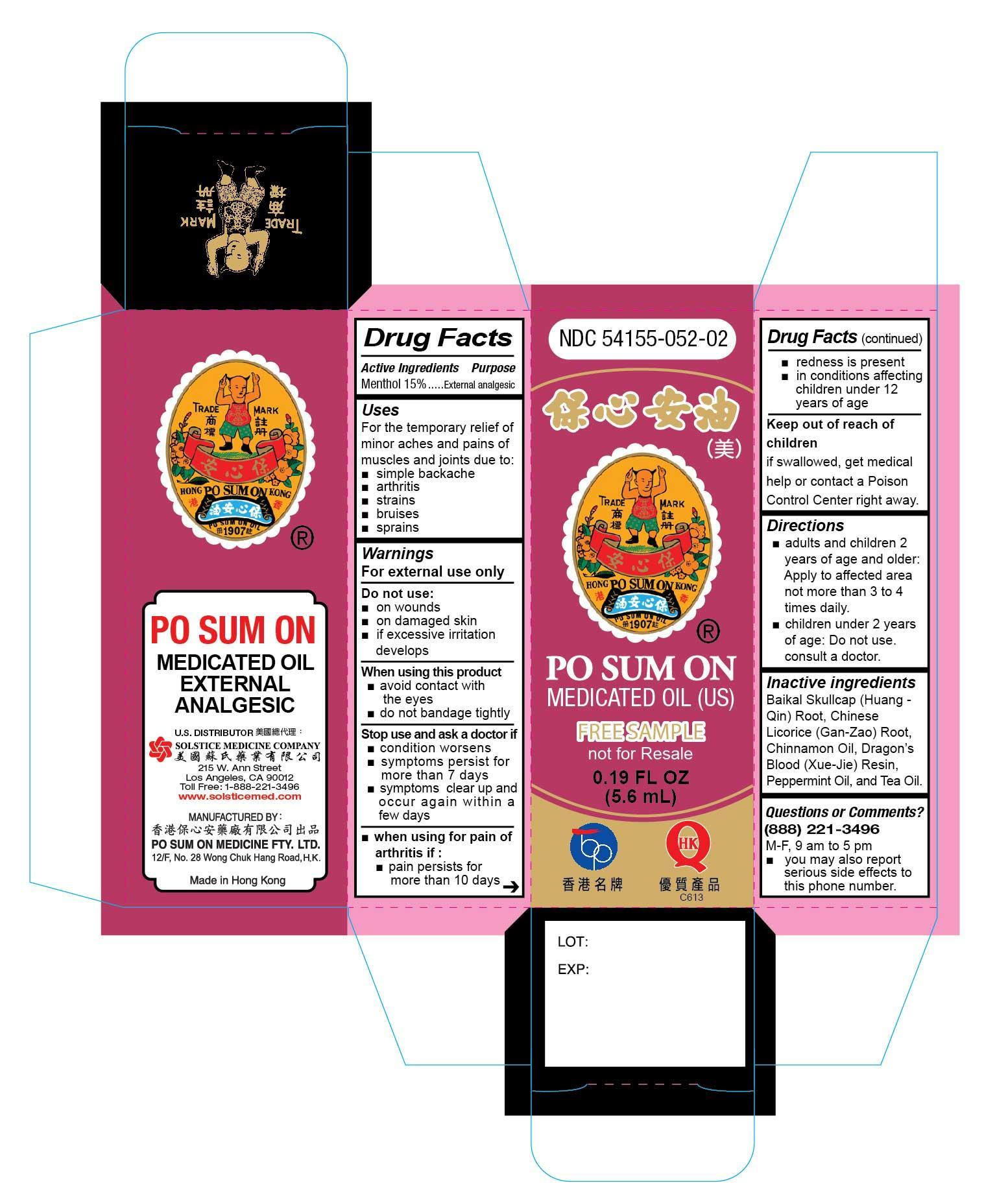 DRUG LABEL: PO SUM ON MEDICATED
NDC: 54155-052 | Form: OIL
Manufacturer: PO SUM ON MEDICINE FACTORY LIMITED
Category: otc | Type: HUMAN OTC DRUG LABEL
Date: 20251110

ACTIVE INGREDIENTS: MENTHOL 15 g/100 mL
INACTIVE INGREDIENTS: SCUTELLARIA BAICALENSIS ROOT; GLYCYRRHIZA URALENSIS WHOLE; CINNAMON OIL; DAEMONOROPS DRACO RESIN; PEPPERMINT OIL; CAMELLIA OIL

Drug Facts

Active ingredients
Menthol 15%

Purpose
External analgesic

Uses
For the temporary relief of minor aches and pains of muscles and joints due to:
simple backache
arthritis
strains
bruises
sprains

Warnings
For external use only

Do not use
on wounds
on damaged skin
if excessive irritation develops

When using this product
avoid contact with the eyes
do not bandage tightly

Stop use and ask a doctor if
condition worsens
symptoms persist for more than 7 days
symptoms clear up and occur again within a few days
when using for pain of arthritis if:
pain persists for more than 10 days
redness is present
in conditions affecting children under 12 years of age

Keep out of reach of children.
If swallowed, get medical help or contact a Poison Control Center right away.

Directions
Adults and children 2 years of age and older: Apply to affected area not more than 3 to 4 times daily.
Children under 2 years of age: Do not use, consult your doctor

Other information
keep container tightly closed
store at 15 to 30C (59 to 86F)

Inactive ingredients
BaikaL Skullcap (Huang-Qin) Root, Chinese Licorice (Gan-Zao) Root, Cinnamon Oil, Dragon’s Blood (Xue-Jie) Resin, Peppermint Oil, and Tea Oil.

Questions or comments? (888)221-3496 M-F 9am to 5pm
you may also report serious side effects to this phone number

PACKAGE LABEL

PO SUM ON MEDICATED OIL, EXTERNAL ANALGESIC, NDC 54155-052-02, FREE SAMPLE, NOT FOR RESALE, 0.19 fl. oz (5.6 ML)

PACKAGE LABEL

PO SUM ON MEDICATED OIL, EXTERNAL ANALGESIC, NDC 54155-052-01 Net wt. 1 fl. oz (30ml.)